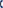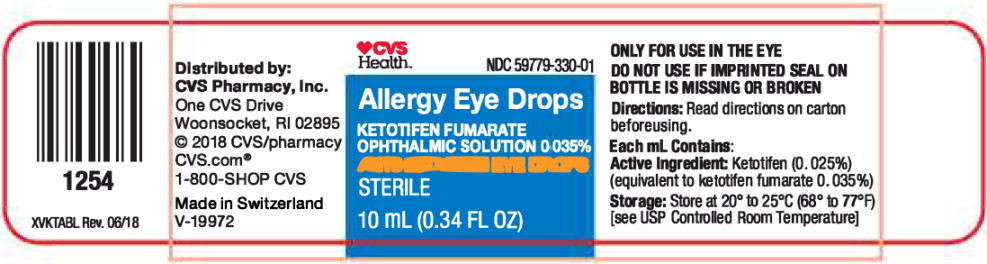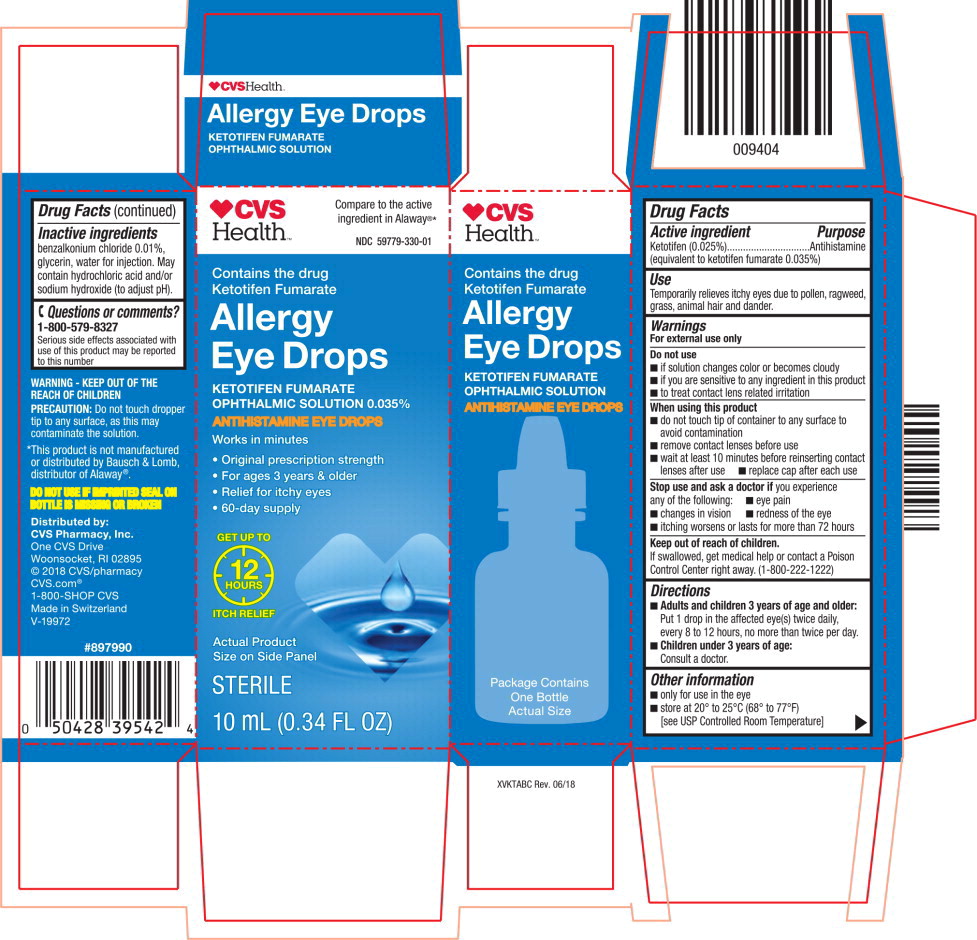 DRUG LABEL: Ketotifen Fumarate
NDC: 59779-330 | Form: SOLUTION/ DROPS
Manufacturer: CVS Pharmacy
Category: otc | Type: HUMAN OTC DRUG LABEL
Date: 20220210

ACTIVE INGREDIENTS: ketotifen fumarate 0.35 mg/1 mL
INACTIVE INGREDIENTS: benzalkonium chloride; glycerin; water; hydrochloric acid; sodium hydroxide

Drug Facts

Active ingredient

Ketotifen (0.025%)

(equivalent to ketotifen fumarate 0.035%)

Purpose

Antihistamine

Use

Temporarily relieves itchy eyes due to pollen, ragweed, grass, animal hair and dander.

Warnings

For external use only

Do not use

- if solution changes color or becomes cloudy
- if you are sensitive to any ingredient in this product
- to treat contact lens related irritation

When using this product

- do not touch tip of container to any surface to avoid contamination
- remove contact lenses before use
- wait at least 10 minutes before reinserting contact lenses after use
- replace cap after each use

Stop use and ask a doctor if you experience any of the following:

- eye pain
- changes in vision
- redness of the eye
- itching worsens or lasts for more than 72 hours

Keep out of reach of children.

If swallowed, get medical help or contact a Poison Control Center right away. (1-800-222-1222)

Directions

- Adults and children 3 years of age and older:
  Put 1 drop in the affected eye(s) twice daily, every 8 to 12 hours, no more than twice per day.
- Children under 3 years of age: Consult a doctor.

Other information

- only for use in the eye
- store at 20° to 25°C (68° to 77°F) [see USP Controlled Room Temperature]

Inactive ingredients

benzalkonium chloride 0.01%, glycerin, water for injection. May contain hydrochloric acid and/or sodium hydroxide (to adjust pH).

Questions or comments?

1-800-579-8327

Serious side effects associated with use of this product may be reported to this number

Principal Display Panel Text for Container Label:

CVS Health™ Logo NDC 59779-330-01

Allergy Eye Drops

KETOTIFEN FUMARATE

OPHTHALMIC SOLUTION 0.035%

ANTIHISTAMINE EYE DROPS

STERILE

10 mL (0.34 FL OZ)

Principal Display Panel Text for Carton Label:

CVS Health™ Logo Compare to the active

ingredient in Alaway®*

NDC 59779-330-01

Contains the drug

Ketotifen Fumarate

Allergy

Eye Drops

KETOTIFEN FUMARATE

OPHTHALMIC SOLUTION 0.035%

ANTIHISTAMINE EYE DROPS

Works in minutes

• Original prescription strength

• For ages 3 years & older

• Relief for itchy eyes

• 60-day supply

GET UP TO

12

HOURS

ITCH RELIEF

Actual Product

Size on Side Panel

STERILE

10 mL (0.34 FL OZ)